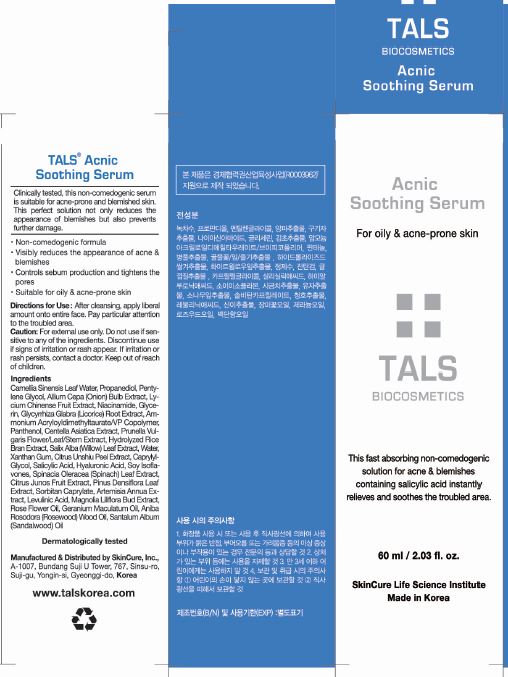 DRUG LABEL: Tals Acnic Soothing Serum
NDC: 72289-0002 | Form: LIQUID
Manufacturer: SKINCURE INC
Category: otc | Type: HUMAN OTC DRUG LABEL
Date: 20190223

ACTIVE INGREDIENTS: SALICYLIC ACID 0.2 g/100 mL
INACTIVE INGREDIENTS: PANTHENOL; NIACINAMIDE; WATER

Drug Facts

ACTIVE INGREDIENT

salicylic acid

INACTIVE INGREDIENT

Camellia Sinensis Leaf Water
Propanediol
Pentylene Glycol
Allium Cepa (Onion) Bulb Extract
Lycium Chinense Fruit Extract
Niacinamide
Glycerin
Glycyrrhiza Glabra (Licorice) Root Extract
Ammonium Acryloyldimethyltaurate/VP Copolymer
Panthenol
Centella Asiatica Extract
Prunella Vulgaris Flower/Leaf/Stem Extract
Hydrolyzed Rice Bran Extract
Salix Alba (Willow) Leaf Extract
Water(Aqua)
Xanthan Gum
Citrus Unshiu Peel Extract
Caprylyl Glycol
Salicylic Acid
Hyaluronic Acid
Soy Isoflavones
Spinacia Oleracea (Spinach) Leaf Extract
Citrus Junos Fruit Extract
Pinus Densiflora Leaf Extract
Sorbitan Caprylate
Artemisia Annua Extract
Levulinic Acid
Magnolia Liliflora Bud Extract
Aniba Rosodora (Rosewood) Wood Oil
Geranium Maculatum Oil
Santalum Album (Sandalwood) Oil
Rose Flower Oil

PURPOSE

visibly reduces the appearance of acne & blemishes

controls sebum production and tightens the pores

suitabgle for oily & acne-prone skin

keep out of reach of the children

INDICATIONS AND USAGE

After cleanisng, apply iberal amount onto entire face. Pay particular attention to the troubled area.

WARNINGS

for external use only

do not use if sensitive to any of the ingredients

discontinue use if signs of irritation or rash appear

if irritation or rash persists, contact a doctor

DOSAGE AND ADMINISTRATION

for external use only